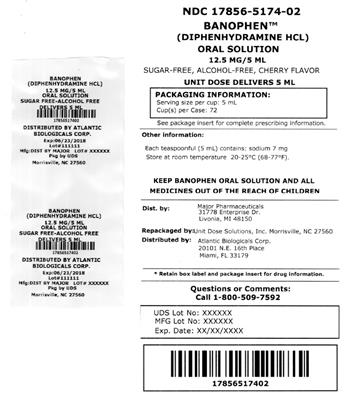 DRUG LABEL: Banophen
NDC: 17856-5174 | Form: LIQUID
Manufacturer: Atlantic Biologicals Corps
Category: otc | Type: HUMAN OTC DRUG LABEL
Date: 20190917

ACTIVE INGREDIENTS: DIPHENHYDRAMINE HYDROCHLORIDE 12.5 mg/5 mL
INACTIVE INGREDIENTS: SODIUM CITRATE, UNSPECIFIED FORM; Citric Acid Monohydrate; Sorbitol; FD&C Red no. 40; Glycerin; Polysorbate 20; Cherry; Water; Sodium Benzoate; SACCHARIN SODIUM; D&C Red no. 33

Banophen

Drug Facts

Active ingredient (in each teaspoonful (5 mL))

Diphenhydramine HCl USP 12.5 mg

Purpose

Antihistamine

Uses

temporarily relieves these symptoms due to hay fever or other upper respiratory allergies

- runny nose
- sneezing
- itchy, watery eyes
- itching of the nose or throat

Warnings

Do not use

- to make a child sleepy
- with any other product containing diphenhydramine, including one applied topically.

Ask a doctor before use if you have

- glaucoma
- trouble urinating due to an enlarged prostate gland
- a breathing problem such as emphysema or chronic bronchitis

Ask a doctor or pharmacist before use if you are taking sedatives or tranquilizers.

When using this product

- marked drowsiness may occur
- avoid alcoholic drinks
- alcohol, sedatives, and tranquilizers may increase drowsiness
- be careful when driving a motor vehicle or operating machinery
- excitability may occur, especially in children

PREGNANCY OR BREAST FEEDING

If pregnant or breast-feeding, ask a health professional before use.

KEEP OUT OF REACH OF CHILDREN

Keep out of the reach of children. In case of overdose, get medical help or contact a Poison Control Center right away.

Directions

- take every 4 to 6 hours
- do not take more than 6 doses in 24 hours

adults and children 12 years and over | 2 - 4 teaspoonsful (25 mg to 50 mg)
children 6 to under 12 years | 1 - 2 teaspoonsful (12.5 mg to 25 mg)
children 2 to 5 years of age | do not use unless directed by a doctor
children under 2 years of age | do not use

Other information

- each teaspoonful (5 mL) contains: sodium 7 mg
- store at room temperature 20°-25°C (68°-77°F)

Inactive ingredients

artificial cherry flavor, citric acid, D&C Red #33, FD&C Red #40, glycerin, polysorbate 20, purified water, sodium benzoate, sodium citrate, sodium saccharin, sorbitol solution

Questions or comments?

(800) 616-2471

HOW SUPPLIED

Product: 17856-5174

NDC: 17856-5174-2 5 mL in a CUP

NDC: 17856-5174-1 10 mL in a CUP, UNIT-DOSE